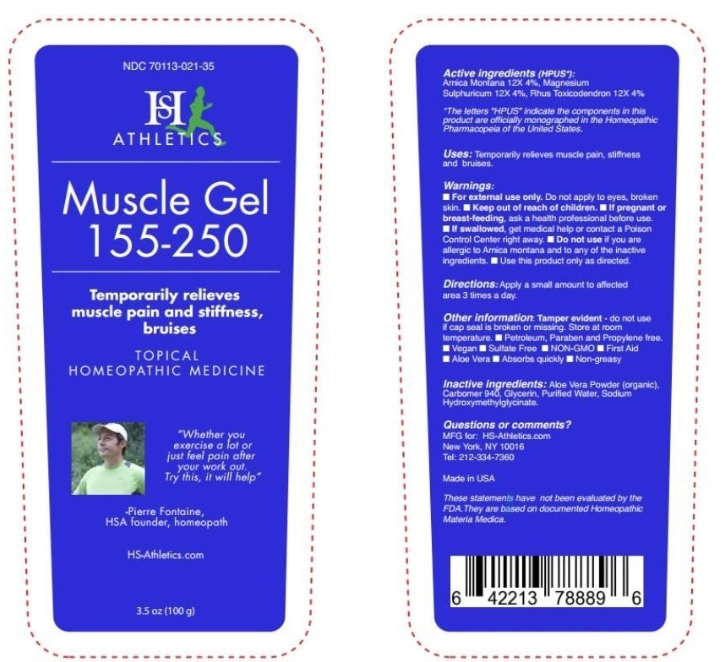 DRUG LABEL: Muscle Gel 155-250
NDC: 70113-021 | Form: GEL
Manufacturer: Homeopathic Services Inc.
Category: homeopathic | Type: HUMAN OTC DRUG LABEL
Date: 20190905

ACTIVE INGREDIENTS: ARNICA MONTANA 12 [hp_X]/1 g; MAGNESIUM SULFATE HEPTAHYDRATE 12 [hp_X]/1 g; TOXICODENDRON PUBESCENS LEAF 12 [hp_X]/1 g
INACTIVE INGREDIENTS: ALOE VERA LEAF; CARBOMER HOMOPOLYMER TYPE C (ALLYL PENTAERYTHRITOL CROSSLINKED); GLYCERIN; WATER; SODIUM HYDROXYMETHYLGLYCINATE

Muscle Gel 155-250

Active ingredients (HPUS*):

Arnica Montana 12X 4%, Magnesium Sulphuricum 12X 4%, Rhus Toxicodendron 12X 4%

ACTIVE INGREDIENT

*The letters "HPUS" indicate the components in this product are officially monographed in the Homeopathic Pharmacopeia of the United States.

INDICATIONS AND USAGE

Uses: Tempoarily relieves muscle pain, stiffness and bruises.

INDICATIONS AND USAGE

These statements have not been evaluated by the FDA. They are based on documented Homeopathic Materia Medica.

Warnings:

- For external use only. Do not apply to eyes, broken skin.
- If pregnant or breast-feeding, ask a health professional before use.
- If swallowed, get medical help or contact a Poison Control Center right away.
- Do not use if you are allergic to Arnica montana and to any of the inactive ingredients.
- Use this product only as directed.

- Keep out of reach of children.

DOSAGE AND ADMINISTRATION

Directions: Apply a small amount to affected area 3 times a day.

Other information: Tamper evident - do not use if cap seal is broken or missing. Store at room temperature.

- Petroleum, Paraben and Propylene free
- Vegan
- Sulfate Free
- NON-GMO
- First Aid
- Aloe Vera
- Absorbs quickly
- Non-greasy

INACTIVE INGREDIENT

Inactive ingredients: Aloe Vera Powder (organic), Carbomer 940. Glycerin, Purified Water, Sodium Hydroxymethylglycinate.

Questions or comments?

MFG for: HS-Athletics.com

New York, NY 10016

Tel: 212-334-7360

Made in the USA

PACKAGE LABEL

NDC 7011-021-35

ATHLETICS

Muscle Gel

155-250

Temporarily relieves

muscle pain and stiffness,

bruises

TOPICAL

HOMEOPATHIC MEDICINE

"

exercise a lot or

just feel pain after

your work out."

Try this, it will help"

- Pierre Fontaine,

HSA founder, homeopath

HS-Athletics.com

3.5 oz (100 g)

PURPOSE

Temporarily relieves muscle pain, stiffness and bruises.